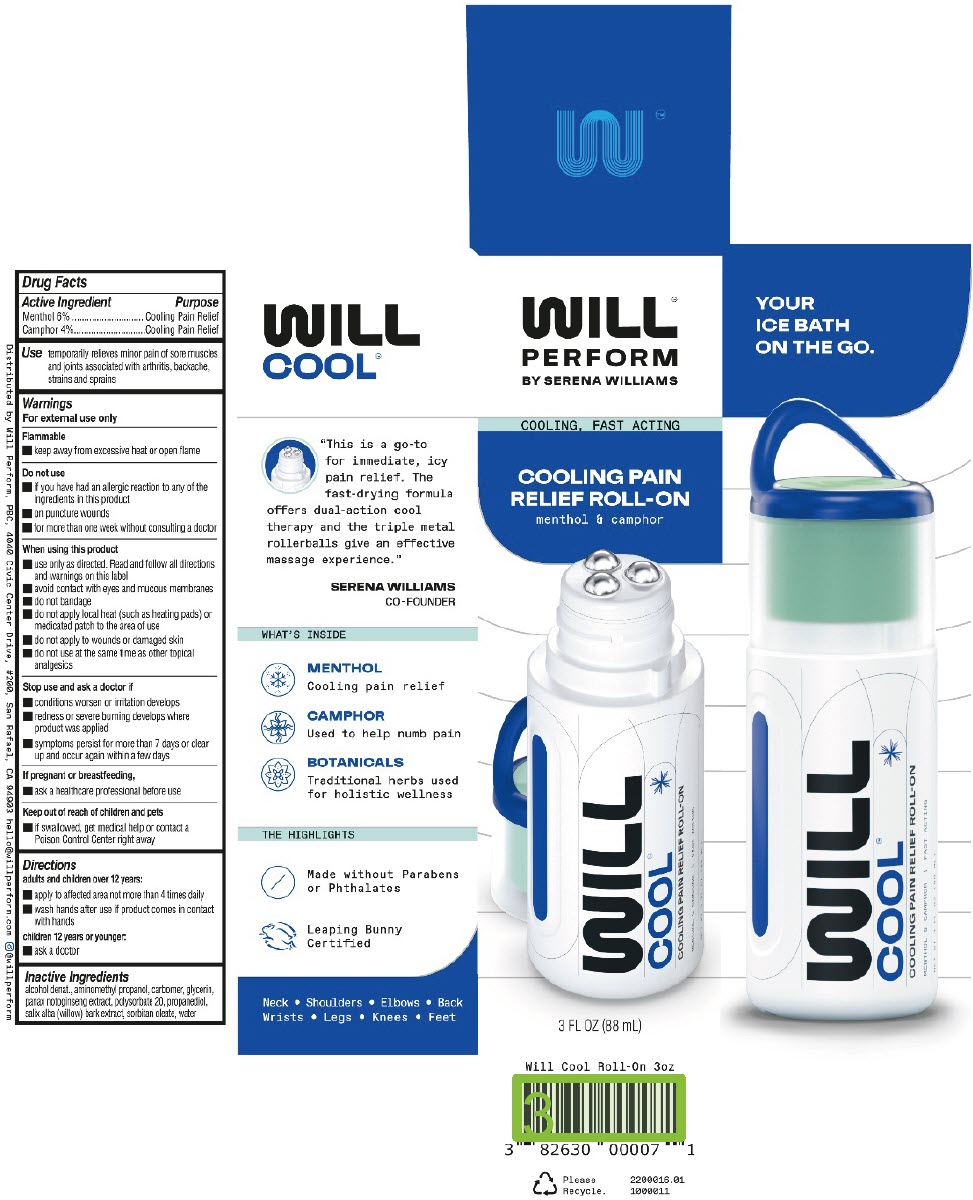 DRUG LABEL: Will Cool Roll-On
NDC: 82630-004 | Form: GEL
Manufacturer: Will Perform, PBC
Category: otc | Type: HUMAN OTC DRUG LABEL
Date: 20231006

ACTIVE INGREDIENTS: CAMPHOR (SYNTHETIC) 3.3 g/88 mL; MENTHOL, UNSPECIFIED FORM 5 g/88 mL
INACTIVE INGREDIENTS: ALCOHOL; AMINOMETHYLPROPANOL; CARBOMER COPOLYMER TYPE B (ALLYL PENTAERYTHRITOL CROSSLINKED); GLYCERIN; PANAX NOTOGINSENG ROOT; POLYSORBATE 20; PROPANEDIOL; SALIX ALBA BARK; SORBITAN MONOOLEATE; WATER

Will Cool™ Roll-On

Drug Facts

ACTIVE INGREDIENT

Active Ingredient | Purpose
Menthol 6% | Cooling Pain Relief
Camphor 4% | Cooling Pain Relief

Use

temporarily relieves minor pain of sore muscles and joints associated with arthritis, backache, strains and sprains

Warnings

For external use only

Flammable

- keep away from excessive heat or open flame

Do not use

- if you have had an allergic reaction to any of the ingredients in this product
- on puncture wounds
- for more than one week without consulting a doctor

When using this product

- use only as directed. Read and follow all directions and warnings on this label
- avoid contact with eyes and mucous membranes
- do not bandage
- do not apply local heat (such as heating pads) or medicated patch to the area of use
- do not apply to wounds or damaged skin
- do not use at the same time as other topical analgesics

Stop use and ask a doctor if

- conditions worsen or irritation develops
- redness or severe burning develops where product was applied
- symptoms persist for more than 7 days or clear up and occur again within a few days

PREGNANCY OR BREAST FEEDING

If pregnant or breastfeeding,

- ask a healthcare professional before use

Keep out of reach of children and pets

- if swallowed, get medical help or contact a Poison Control Center right away

Directions

adults and children over 12 years:

- apply to affected area not more than 4 times daily
- wash hands after use if product comes in contact with hands

children 12 years or younger:

- ask a doctor

Inactive Ingredients

alcohol denat., aminomethyl propanol, carbomer, glycerin, panax notoginseng extract, polysorbate 20, propanediol, salix alba (willow) bark extract, sorbitan oleate, water

Distributed by Will Perform, PBC,
4040 Civic Center Drive, #200,
San Rafael, CA 94903

PRINCIPAL DISPLAY PANEL - 88 mL Bottle Carton

WILL™
PERFORM
BY SERENA WILLIAMS

COOLING, FAST ACTING

COOLING PAIN
RELIEF ROLL-ON

menthol & camphor

3 FL OZ (88 mL)